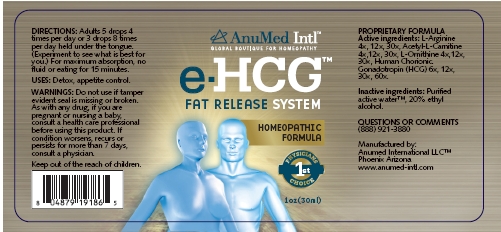 DRUG LABEL: e-HCG
NDC: 50970-001 | Form: LIQUID
Manufacturer: AnuMed International LLC
Category: homeopathic | Type: HUMAN OTC DRUG LABEL
Date: 20231129

ACTIVE INGREDIENTS: ARGININE 30 [hp_X]/30 mL; ACETYLCARNITINE 30 [hp_X]/30 mL; ORNITHINE 30 [hp_X]/30 mL; HUMAN CHORIONIC GONADOTROPIN 60 [hp_X]/30 mL
INACTIVE INGREDIENTS: ALCOHOL 30 mL/30 mL; WATER 30 mL/30 mL

e-HCG
FAT RELEASE SYSTEM
HOMEOPATHIC FORMULA

ACTIVE INGREDIENTS:

L-Arginine 3x, 12x, 30x

Acetyl-L-Carnitine 3x, 12x, 30x

L-Ornithine 3x, 12x, 30x

Human Chorionic Gonadotropin (HCG) 6x, 12x, 30x, 60x

PURPOSE:

Detox, appetite control

USES:

Detox, appetite control

WARNINGS:

Do Not Use

if tamper evident seal is missing or broken.

Pregnancy or Breast Feeding

As with any drug, it you are pregnant or nursing a baby, consult a health care professional before using this product.

Ask Doctor

If condition worsens, recurs or persists for more than 7 days, consult a physician.

DIRECTIONS:

Adults 5 drops 4 times per day or 3 drops 8 times per day held under the tongue. (Experiment to see what is best for you.) For maximum absorption, no fluid or eating for 15 minutes.

INACTIVE INGREDIENTS:

Purified active water, 20% ethyl alcohol.

QUESTIONS OR COMMENTS

(888) 921-3880

Manufactured by:
Anumed International LLC™
Phoenix Arizona
www.anumed-intl.com

PACKAGE/LABEL PRINCIPAL DISPLAY PANEL

AnuMed Intl™

Global Boutique for Homeopathy

e-HCG

FAT RELEASE SYSTEM

HOMEOPATHIC FORMULA

Physicians 1st Choice

1oz(30ml)